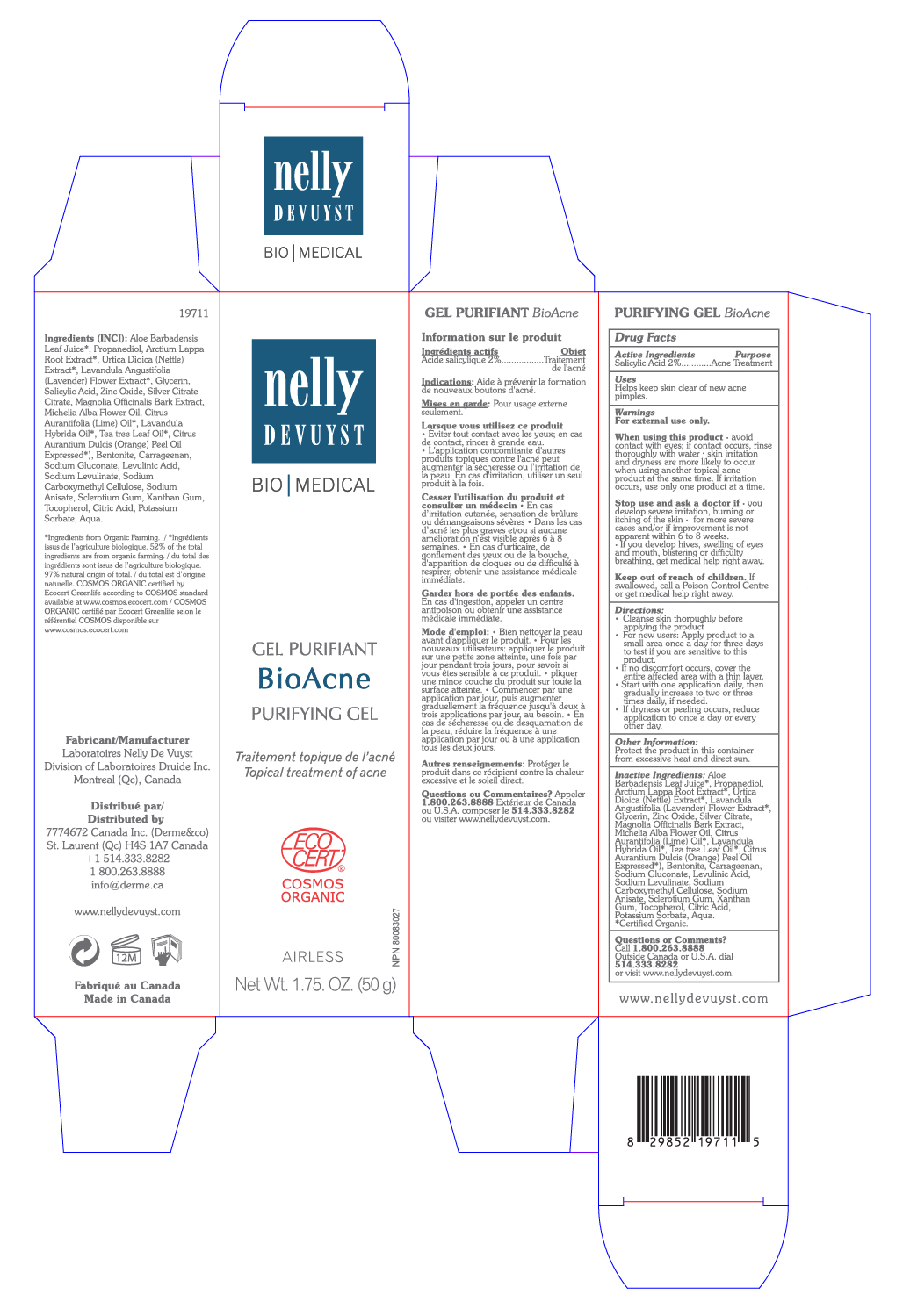 DRUG LABEL: NELLY DEVUYST PURIFYING BIOACNE
NDC: 71447-004 | Form: GEL
Manufacturer: LABORATOIRES DRUIDE INC
Category: otc | Type: HUMAN OTC DRUG LABEL
Date: 20210101

ACTIVE INGREDIENTS: SALICYLIC ACID 2 g/100 g
INACTIVE INGREDIENTS: MICHELIA ALBA LEAF OIL; SILVER CITRATE; MAGNOLIA OFFICINALIS BARK; LAVANDIN OIL; CITRUS AURANTIUM FRUIT OIL; BENTONITE; CARRAGEENAN; GLYCERIN; SODIUM GLUCONATE; LEVULINIC ACID; SODIUM LEVULINATE; PROPANEDIOL; URTICA DIOICA LEAF; CARBOXYMETHYLCELLULOSE SODIUM; SODIUM ANISATE; BETASIZOFIRAN; CITRIC ACID MONOHYDRATE; POTASSIUM SORBATE; WATER; XANTHAN GUM; TOCOPHEROL; LIME OIL; TEA TREE OIL; LAVANDULA ANGUSTIFOLIA FLOWER; ZINC OXIDE; ALOE VERA LEAF; ARCTIUM LAPPA ROOT

NELLY DEVUYST PURIFYING GEL BIOACNE 50g

Active Ingredient

Salicylic Acid 2%

Purpose

Acne Treatment

Uses

Helps keep skin clear of new acne pimples.

Warnings

For external use only.

When using this product

▪ avoid contact with eyes. If contact occurs, rinse thoroughly with water ▪ Skin irritation and dryness are more likely to occur when using another topical acne product at the same time. If irritation occurs, use only one product at a time.

and ask a doctor if

▪ you develop severe irritation, burning or itching of the skin ▪ for more severe cases and or if improvement is not apparent within 6 to 8 weeks ▪ If you develop hives, swelling of eyes and mouth, blistering or difficulty breathing, get medical help right away.

Keep out of reach of children

If swallowed, get medical help or contact a Poison Control Center right away.

Directions

▪ Cleanse skin thoroughly before applying the product.

▪ For new users: apply product to a small area once a day for three days to test if you are sensitive to this product.

▪ If no discomfort occurs, cover the entire affected area with a thin layer.

▪ Start with one application daily, then gradually increase to two or three times daily, if needed.

▪ If dryness or peeling occurs, reduce application to once a day or every other day.

Other Information

Protect the product in this container from excessive heat and direct sun.

Inactive Ingredients

Aloe Barbadensis Leaf Juice*, Propanediol, Arctium Lappa Root Extract*, Urtica Dioica (Nettle) Extract*, Lavandula Angustifolia (Lavender) Flower Extract*, Glycerin, Zinc Oxide, Silver Citrate, Magnolia Officinalis Bark Extract, Michelia Alba Flower Oil, Citrus Aurantifolia (Lime) Oil*, Lavandula Hybrida Oil*, Tea Tree Leaf Oil*, Citrus Aurantium Dulcis (Orange) Peel Oil Expressed*, Bentonite, Carrageenan, Sodium Gluconate, Levulinic Acid, Sodium Levulinate, Sodium Carboxymethyl Cellulose, Sodium Anisate, Sclerotium Gum, Xanthan Gum, Tocopherol, Citric Acid, Potassium Sorbate, Aqua.

* Certified organic.

Questions or Comments?

+1 800-263-8888

Outside Canada or United States, dial +1 514-333-8282, or visit www.nellydevuyst.com

Distributed By

7774672 Canada Inc (Derme & Co)

4980 Chemin Bois Franc

St. Laurent, QC H4S 1A7

Canada

+1 514-333-8282, +1 800-263-8888

www.nellydevuyst.com

Made in Canada